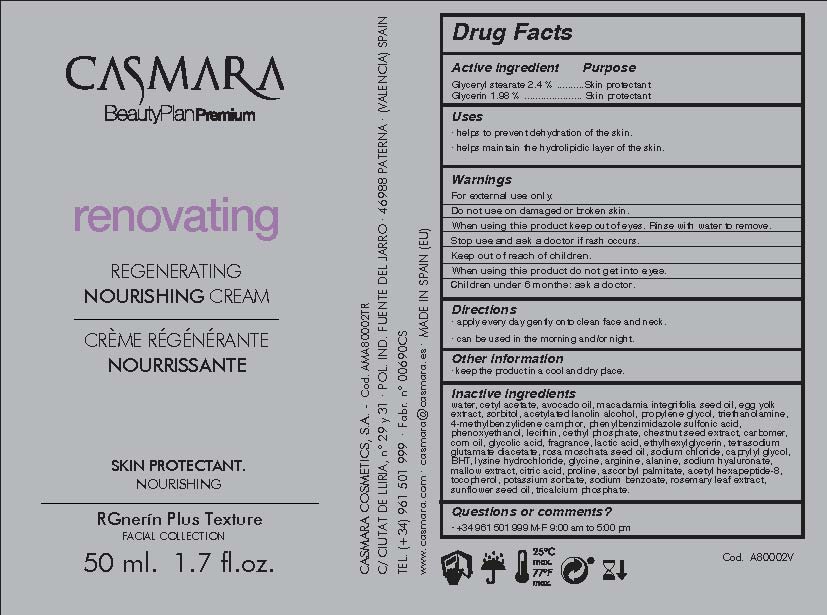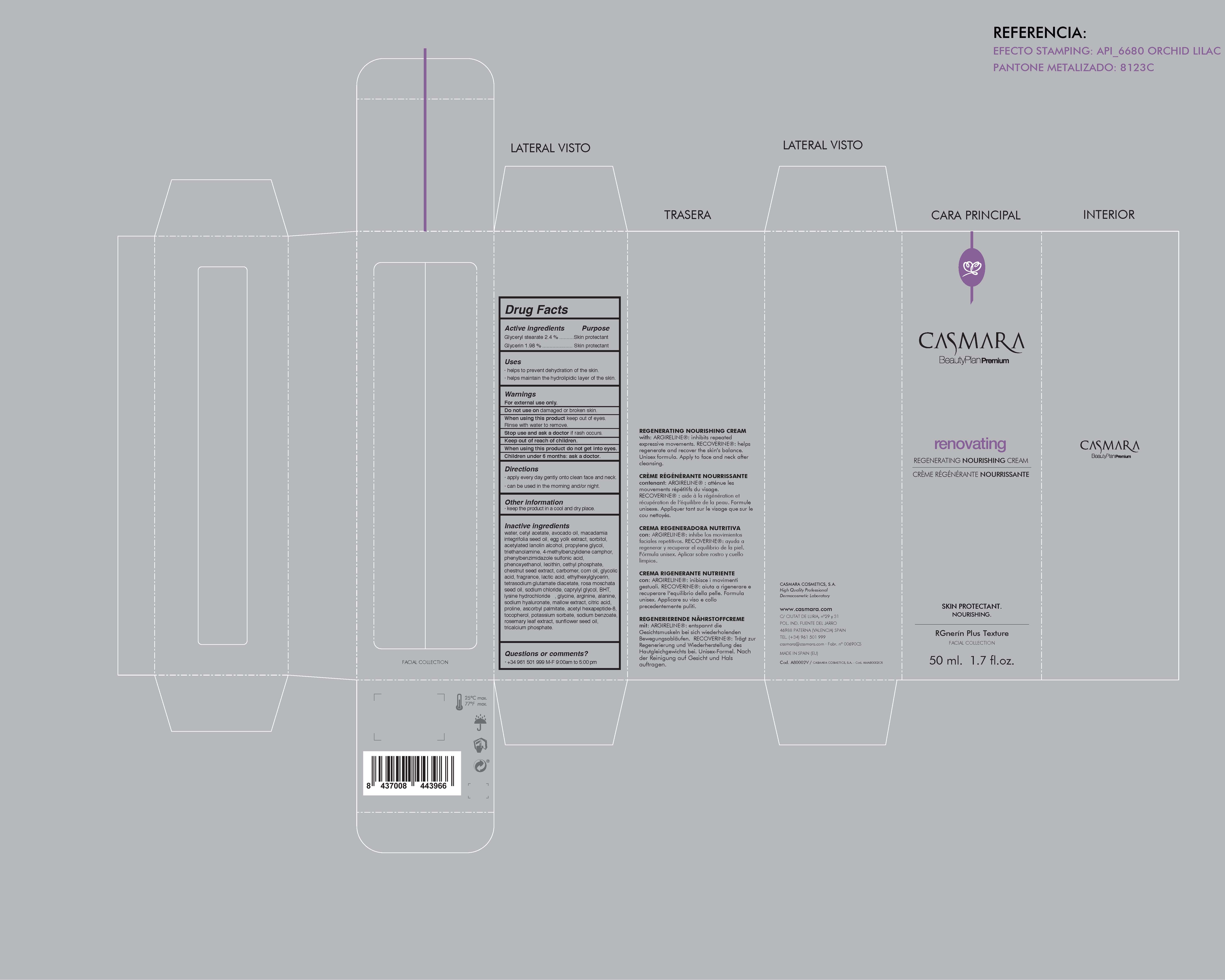 DRUG LABEL: Renovating Regenerating Nourishing Cream
NDC: 20151-085 | Form: CREAM
Manufacturer: Casmara Cosmetics, SA
Category: otc | Type: HUMAN OTC DRUG LABEL
Date: 20170223

ACTIVE INGREDIENTS: GLYCERIN 1.98 mg/1 mL
INACTIVE INGREDIENTS: SPANISH CHESTNUT 0.5 mg/1 mL; ROSA MOSCHATA OIL 0.062 mg/1 mL; SODIUM CHLORIDE 0.033 mg/1 mL; GLYCOLIC ACID 0.21 mg/1 mL; CAPRYLYL GLYCOL 0.025 mg/1 mL; LYSINE HYDROCHLORIDE 0.022 mg/1 mL; GLYCINE 0.022 mg/1 mL; ASCORBYL PALMITATE 0.0034 mg/1 mL; SODIUM BENZOATE 0.0016 mg/1 mL; ROSEMARY 0.0012 mg/1 mL; CETYL PHOSPHATE 0.75 mg/1 mL; ETHYLHEXYLGLYCERIN 0.111 mg/1 mL; WATER 58.029 mg/1 mL; PHENOXYETHANOL 0.94 mg/1 mL; TETRASODIUM GLUTAMATE DIACETATE 0.1 mg/1 mL; TOCOPHEROL 0.0025 mg/1 mL; PERFLUNAFENE 0.2 mg/1 mL; POTASSIUM SORBATE 0.0016 mg/1 mL; TROLAMINE 1.6 mg/1 mL; DIPROPYLENE GLYCOL 1.65 mg/1 mL; LECITHIN, SOYBEAN 0.75 mg/1 mL; TRICALCIUM PHOSPHATE 0.00011 mg/1 mL; ARGININE 0.011 mg/1 mL; HYALURONATE SODIUM 0.1 mg/1 mL; CITRIC ACID MONOHYDRATE 0.008 mg/1 mL; PROLINE 0.0055 mg/1 mL; CETYL ACETATE 11.31 mg/1 mL; AVOCADO OIL 7 mg/1 mL; SORBITOL 2 mg/1 mL; MACADAMIA OIL 4.99 mg/1 mL; ACETYLATED LANOLIN ALCOHOLS 1.69 mg/1 mL; CARBOXYPOLYMETHYLENE 0.5 mg/1 mL; ALANINE 0.011 mg/1 mL; MALVA SYLVESTRIS LEAF 0.0099 mg/1 mL; ACETYL HEXAPEPTIDE-8 0.0025 mg/1 mL; CORN OIL 0.43 mg/1 mL; SUNFLOWER OIL 0.0012 mg/1 mL; LACTIC ACID 0.18 mg/1 mL; GLYCERYL STEARATE SE 2.4 mg/1 mL; EGG YOLK 2.4 mg/1 mL; BUTYLATED HYDROXYTOLUENE 0.022 mg/1 mL

Renovating Regenerating Nourishing Cream

WARNINGS

For external use only.

Do not use on damaged or broken skin.

When using this product keep our of the eyes. Rinse with water to remove.

Stop use and ask a doctor if rash occurs.

Keep out of reach of children.

Whhen using this product do not get into eyes.

Children under 6 months: as a doctor.

Stop use and ask a doctor if rash occurs

Children under 6 months: ask a doctor

. keep out of reach of children

Questions or comments? + 34 961 501 099 M-F 9:00 am to 5:00 pm

OTHER SAFETY INFORMATION

. keep the product in a cool and dry place

Directions

. apply every day gently onto clean face and neck

. can be used in the morning and/or night

DOSAGE AND ADMINISTRATION

. apply every day gently onto clean dace and neck

. can be used in the morning and/or night

Uses

. helps to prevent dehydration of the skin.

. helps maintain the hydrolipidic layer of the skin

INACTIVE INGREDIENT

Water, Cetyl acetate, Avocado oil, Macadamia integrifolia seed oil, Egg yolk extract, Glyceryl stearate, Sorbitol, Acetylated lanolin, alcohol, Propylene glycol, Triethanolamine, 4-methylbenzylidene camphor, Phenylbenzimidazole sulfonic acid, Phenoxyethanol, Lecithin, Cethyl phosphate, Chestnut seed extract, Carbomer, Corn oil, Glycolic acid, Fragrance, Lactic acid, Ethylhexylglycerin, Tetrasodium glutamate diacetate, Rosa moschata seed oil, Sodium chloride, Caprylyl glycol, BHT, Lysine hydrochloride, Glycinel Arginine, Alanine, Sodium hyaluronate, Mallow extract, Citric acid, Proline, Ascorbyl palmitate, Acetyl hexapeptide-8l Tocopherol, Potassium sorbate, Sodium benzoate, Rosemary leaf extract, Sunflower seed oil, Tricalcium phosphate

PURPOSE

. helps to prevent dehydration of the skin

. helps maintain the hydrolipidic layer of the skin

Active Ingredients

Glycerin 1.98%........................... Skin Protectant

PACKAGE LABEL

Renovating

Regenerating Nourishing Cream

Skin Protectant

Moisturizing

RGnerin Plus Texture

Facial Collection